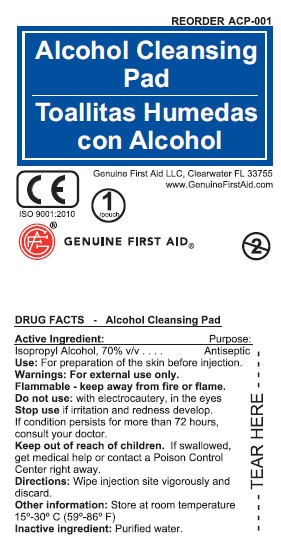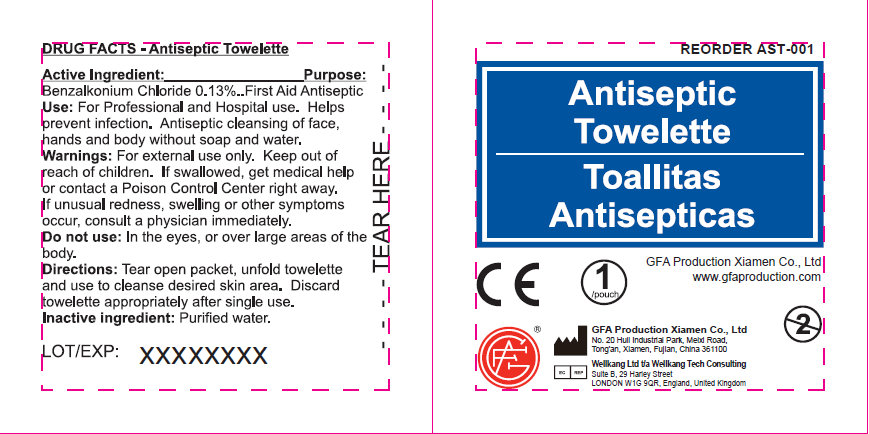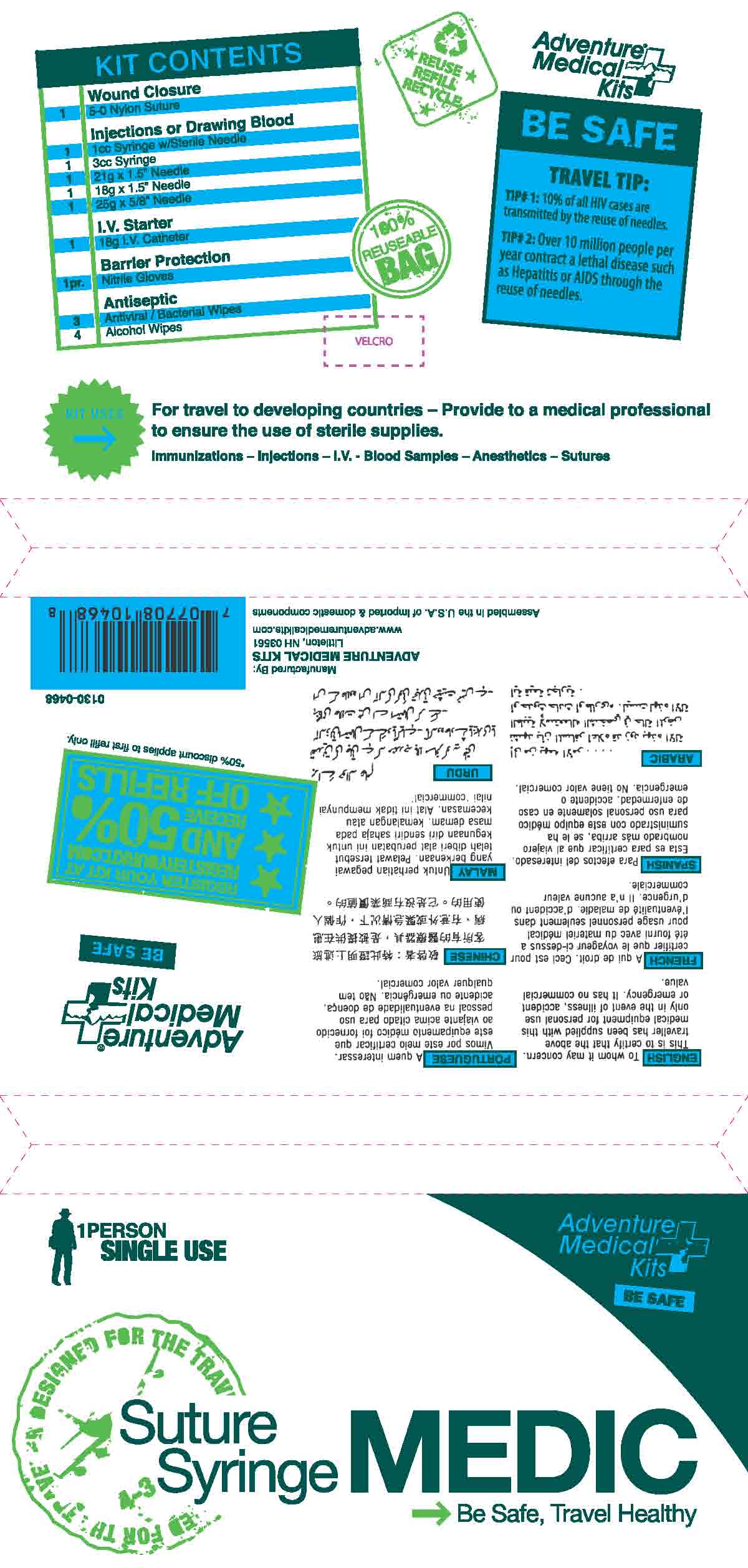 DRUG LABEL: Suture Syringe Medic
NDC: 44224-0468 | Form: KIT | Route: TOPICAL
Manufacturer: Tender Corporation
Category: otc | Type: HUMAN OTC DRUG LABEL
Date: 20170316

ACTIVE INGREDIENTS: ISOPROPYL ALCOHOL 700 mg/1 mL; BENZALKONIUM CHLORIDE 1.3 mg/1 mL
INACTIVE INGREDIENTS: WATER; WATER

Suture Syringe Medic

Active Ingredient - Antiseptic

Benzalkonium Chloride 0.13%

Purpose - Antiseptic

Antiseptic

Use - Antiseptic

For Professional and hospital use. Helps prevent infection. Antiseptic cleansing of face, hands and body without soap and water.

Warnings, Precautions and Directions - Antiseptic

For External use only.

Keep out of Reach of Children.

Stop use if unusual redness, swelling or other symptoms occur, consult a physician immediately.

Do not uses in eyes or over large areas of the body.

Tear open packet, unfold towelette and use to cleanse desired skin area. Discard towelette appropriately after single use.

Inactive Ingredients - Antiseptic

Purified Water

Active Ingredient - Alcohol Prep Pad

Isopropyl Alcohol 70%

Use - Alcohol Prep Pad

For preparation of the skin before injection

Warnings, Precautions and Directions - Alcohol Prep Pad

For External Use Only

Flammable - Keep away from fire or flame

Do Not Use - with electrocautery, in eyes

Stop Use and Ask a Doctor if - Irritation or redness develop and persists for more than 72 hours

Keep out of Reach of Children

If swallowed, get medical help or contact a poison control center right away.

Tear Open packet, unfold and use as and wipe injection site vigorously and discard.

Store at Room Temperature

Keep out of Reach of Children